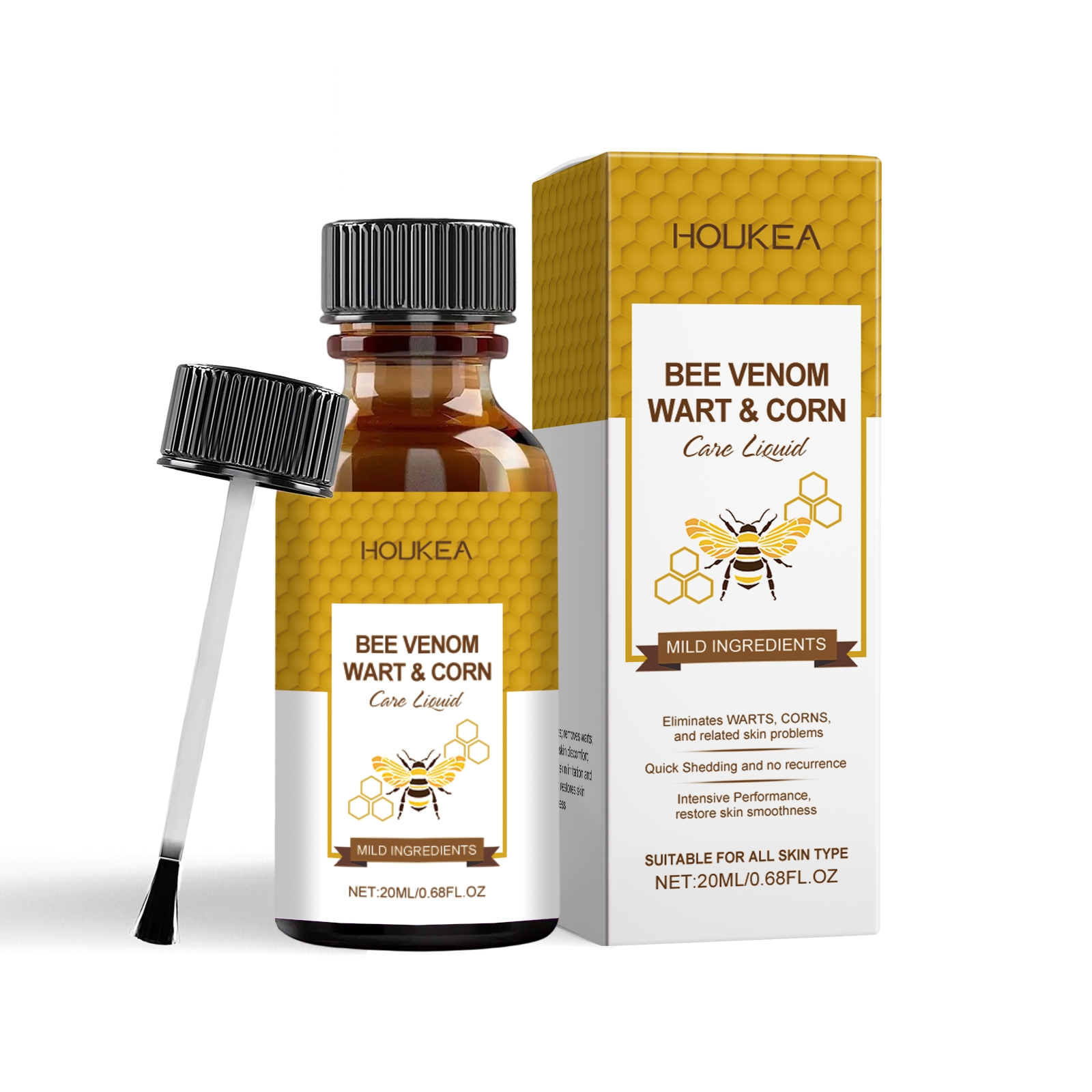 DRUG LABEL: HOUKEA Wart Corn Care Liquid
NDC: 84984-004 | Form: LIQUID
Manufacturer: Guangzhou Houkea Biotechnology Co., Ltd.
Category: otc | Type: HUMAN OTC DRUG LABEL
Date: 20251127

ACTIVE INGREDIENTS: APIS MELLIFERA VENOM 0.004 mg/20 mg; MENTHA PIPERITA LEAF 0.004 mg/20 mg
INACTIVE INGREDIENTS: GLYCERIN 1.6 mg/20 mg; HYDROXYMETHYL CELLULOSE 0.1 mg/20 mg; ALLANTOIN 0.004 mg/20 mg; WATER 18.288 mg/20 mg

ACTIVE INGREDIENT

APIS MELLIFERA VENOM、MENTHA PIPERITA LEAF

WHEN USING

Clean and dry the skin, apply an appropriate amount of this product evenly on the affected skin, and gently massage until absorbed.

PURPOSE

Exfoliates; removes warts; soothes skin discomfort; reduces skin irritation and redness; restores skin smoothness

DO NOT USE

Discontinue use if signs of irritation or rash occur.

STOP USE

Discontinue use if signs of irritation or rash occur.

KEEP OUT OF REACH OF CHILDREN

Please keep out of reach of children. Do not swallow.

WARNINGS

Please keep out of reach of children. Do not swallow.Please clean your hands before use to ensure the best results from the product. Discontinue use if signs of irritation or rash occur. Store in a cool and dry place.

STORAGE AND HANDLING

Store in a cool and dry place.

INACTIVE INGREDIENT

WATER、GLYCERIN、HYDROXYETHYL CELLULOSE、ALLANTOIN